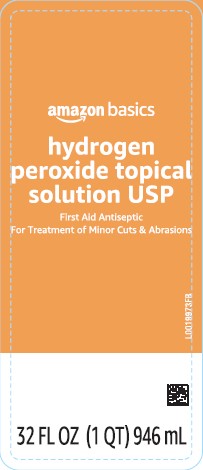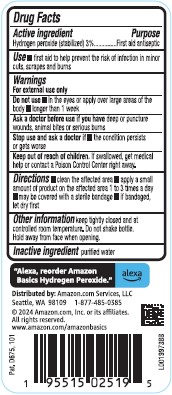 DRUG LABEL: Hydrogen Peroxide
NDC: 72288-871 | Form: SOLUTION
Manufacturer: Amazon.Com Services LLC
Category: otc | Type: HUMAN OTC DRUG LABEL
Date: 20250520

ACTIVE INGREDIENTS: HYDROGEN PEROXIDE 30 mg/1 mL
INACTIVE INGREDIENTS: WATER

Basics 871.001/871AA
3% hydrogen peroxide

Active ingredient

Hydrogen peroxide (stabilized) 3%

Purpose

First aid antiseptic

Use

- first aid to help prevent the risk of infection in minor cuts, scrapes and burns

Warnings

For external use only

Do not use

- in the eyes or apply over large areas of the the body
- longer than 1 week

Ask a doctor before use if you have

deep or puncture wounds, animal bites or serious burns

Stop use and ask a doctor if

- the condition persists or gets worse

Keep out of reach of children.

If swallowed, get medical help or contact a Poison Control Center right away.

Directions

- clean the affected area
- apply a small amount of product on the affected area 1 to 3 times a day
- may be covered with a sterile bandage
- if bandaged, let dry first

Other information

keep tightly closed and at controlled room temperature. Do not shake bottle. Hold away from face when opening.

Inactive ingredient

purified water

Adverse reaction

"Alexa, reorder Amazon Basics Hydrogen Peroxide." alexa

Distributed By: Amazon.com, Services, LLC

Seattle, WA 98109 1-877-485-0385

©2024 Amazon.com, Inc. or its affiliates.

All rights reserved.

www.amazon.com/amazonbasics

Pat. D675,101

Principal display panel

amazon basics

hydrogen peroxide

topical solution USP

First Aid Antiseptic

For Treatment of Minor Cuts & Abrasions

32 FL OZ (1 QT) 946 mL